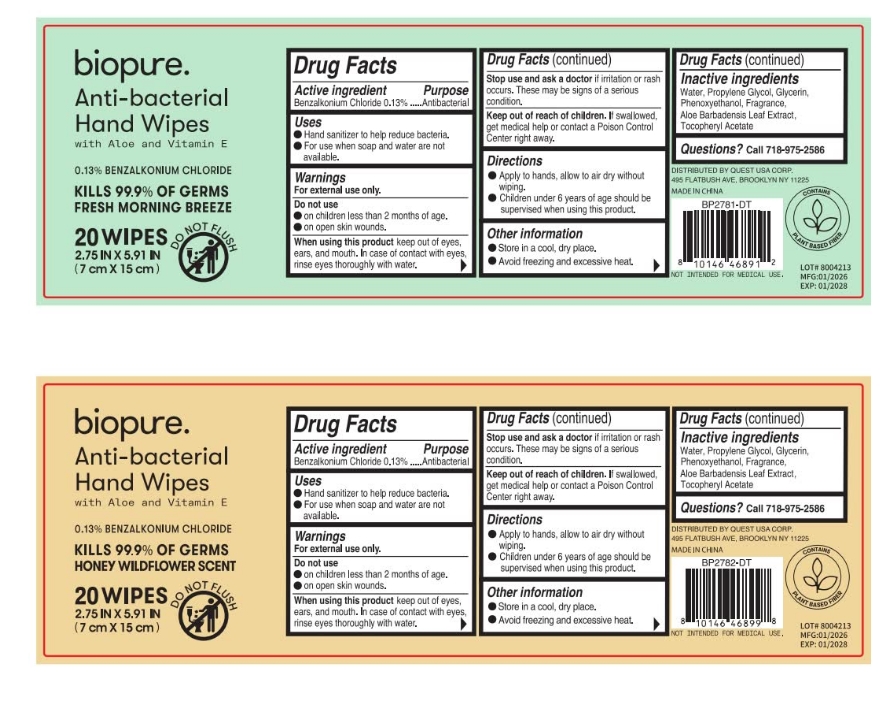 DRUG LABEL: Anti-bacterial Hand Wipes
NDC: 75181-012 | Form: CLOTH
Manufacturer: Jinhua Aidi Daily Chemical Co., Ltd.
Category: otc | Type: HUMAN OTC DRUG LABEL
Date: 20260126

ACTIVE INGREDIENTS: BENZALKONIUM CHLORIDE 0.13 g/100 g
INACTIVE INGREDIENTS: .ALPHA.-TOCOPHEROL ACETATE, D-; PROPYLENE GLYCOL; ALOE BARBADENSIS LEAF; GLYCERIN; PHENOXYETHANOL; WATER

Anti-bacterial Hand Wipes
75181-012-01

Active Ingredient(s)

Benzalkonium Chloride 0.13%

Purpose

Antimicrobial

Use

Hand sanitizer to help reduce bacteria.
For use when soap and water are not available.

Warnings

For external use only.

Do not use

on children less than 2 months old.
on open skin wounds.

When using this product
keep out of eyes, ears, and mouth. In case of contact with eyes, rinse eyes thoroughly with water.

Stop use and ask a doctor if irritation or rash occurs, These may be signs of a serious condition.

Keep out of reach of children. lf swallowed, get medical help or contact a Poison Control Center right away.

Directions

Apply to hands, allow to air dry without wiping.
Children under 6 years of age should be supervised when using this product.

Other information

Store in a cool, dry place.
Avoid freezing and excessive heat.

Inactive ingredients

Water, Propylene Glycol, Glycerin, Phenoxyethanol, Fragrance, Aloe Barbadensis Leaf Extractalky,Tocopheryl Acetate

Package Label - Principal Display Panel

20 wipes in 1 bottle NDC: 75181-012-01